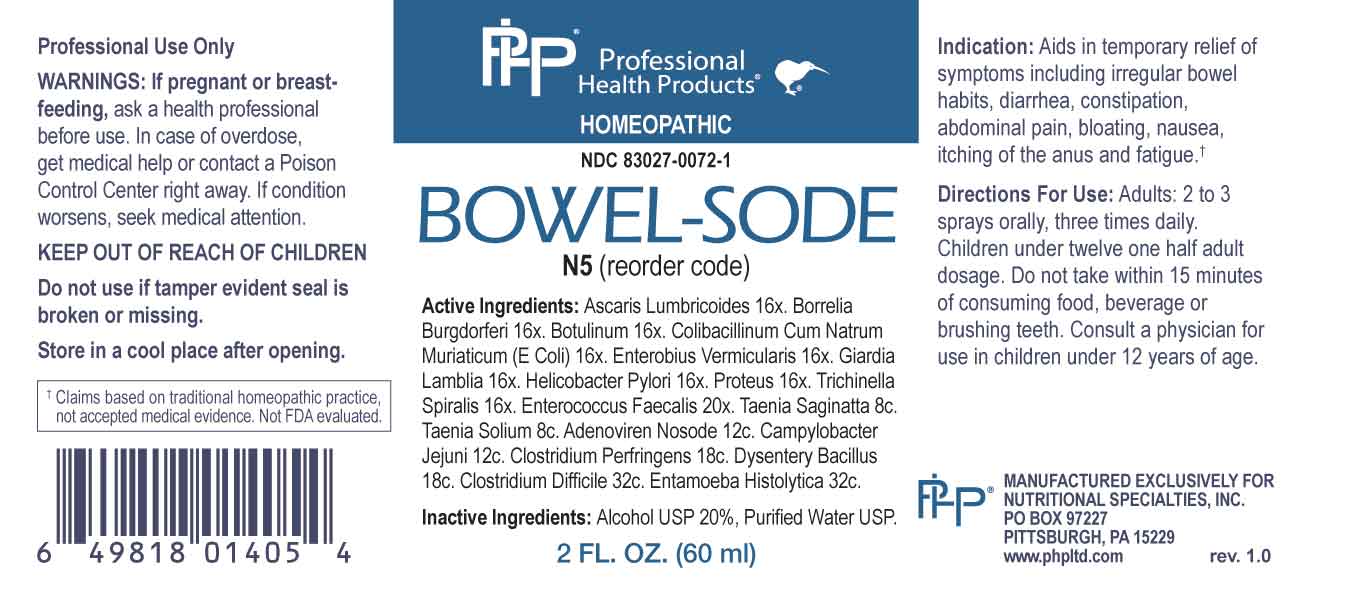 DRUG LABEL: Bowel Sode
NDC: 83027-0072 | Form: SPRAY
Manufacturer: Nutritional Specialties, Inc.
Category: homeopathic | Type: HUMAN OTC DRUG LABEL
Date: 20241031

ACTIVE INGREDIENTS: ASCARIS LUMBRICOIDES 16 [hp_X]/1 mL; BORRELIA BURGDORFERI 16 [hp_X]/1 mL; CLOSTRIDIUM BOTULINUM 16 [hp_X]/1 mL; ESCHERICHIA COLI 16 [hp_X]/1 mL; ENTEROBIUS VERMICULARIS 16 [hp_X]/1 mL; GIARDIA LAMBLIA 16 [hp_X]/1 mL; HELICOBACTER PYLORI 16 [hp_X]/1 mL; PROTEUS VULGARIS 16 [hp_X]/1 mL; TRICHINELLA SPIRALIS 16 [hp_X]/1 mL; ENTEROCOCCUS FAECALIS 20 [hp_X]/1 mL; TAENIA SAGINATA 8 [hp_C]/1 mL; TAENIA SOLIUM 8 [hp_C]/1 mL; HUMAN ADENOVIRUS E SEROTYPE 4 STRAIN CL-68578 ANTIGEN 12 [hp_C]/1 mL; CAMPYLOBACTER JEJUNI 12 [hp_C]/1 mL; CLOSTRIDIUM PERFRINGENS 18 [hp_C]/1 mL; SHIGELLA DYSENTERIAE 18 [hp_C]/1 mL; CLOSTRIDIUM DIFFICILE 32 [hp_C]/1 mL; ENTAMOEBA HISTOLYTICA 32 [hp_C]/1 mL
INACTIVE INGREDIENTS: WATER; ALCOHOL

DRUG FACTS:

ACTIVE INGREDIENTS:

Ascaris Lumbricoides 16X, Borrelia Burgdorferi 16X, Botulinum 16X, Colibacillinum Cum Natrum Muriaticum 16X, Enterobius Vermicularis 16X, Giardia Lamblia 16X, Helicobacter Pylori 16X, Proteus (Vulgaris) 16X, Trichinella Spiralis 16X, Enterococcus Faecalis 20X, Taenia Saginatta 8C, Taenia Solium 8C, Adenoviren Nosode 12C, Campylobacter Jejuni 12C, Clostridium Perfringens 18C, Dysentery Bacillus 18C, Clostridium Difficile 32C, Entamoeba Histolytica 32C.

PURPOSE:

Aids in temporary relief of symptoms including irregular bowel habits, diarrhea, constipation, abdominal pain, bloating, nausea, itching of the anus and fatigue.†

†Claims based on traditional homeopathic practice, not accepted medical evidence. Not FDA evaluated.

WARNINGS:

Professional Use Only

If pregnant or breast-feeding, ask a health professional before use.

In case of overdose, get medical help or contact a Poison Control Center right away.

If condition worsens, seek medical attention.

KEEP OUT OF REACH OF CHILDREN

Do not use if tamper evident seal is broken or missing.

Store in a cool place after opening

KEEP OUT OF REACH OF CHILDREN:

In case of overdose, get medical help or contact a Poison Control Center right away.

DIRECTIONS:

Adults: 2 to 3 sprays orally, three times daily. Children under twelve one half adult dosage. Do not take within 15 minutes of consuming food, beverage or brushing teeth. Consult a physician for use in children under 12 years of age.

INDICATIONS:

Aids in temporary relief of symptoms including irregular bowel habits, diarrhea, constipation, abdominal pain, bloating, nausea, itching of the anus and fatigue.†
†Claims based on traditional homeopathic practice, not accepted medical evidence. Not FDA evaluated.

INACTIVE INGREDIENTS:

Alcohol USP 20%, Purified Water USP.

QUESTIONS:

MANUFACTURED EXCLUSIVELY FOR

NUTRITIONAL SPECIALTIES, INC.

PO BOX 97227

PITTSBURG, PA 15229

www.phpltd.com

PACKAGE LABEL DISPLAY:

Professional

Health Products

HOMEOPATHIC

NDC 83027-0072-1

BOWEL-SODE

2 FL. OZ (60 ml)